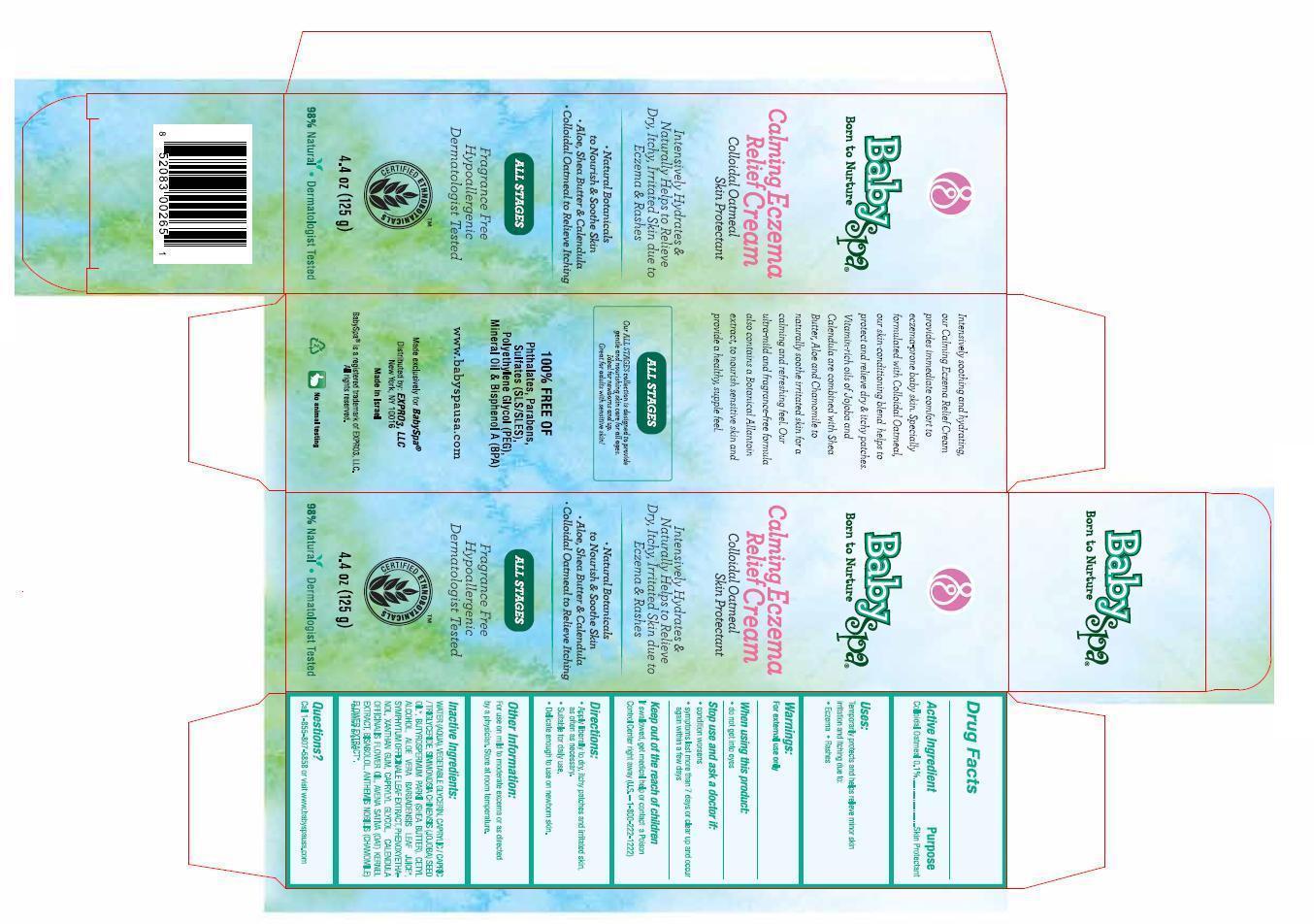 DRUG LABEL: BabySpa Calming Relief Eczema
NDC: 42957-002 | Form: CREAM
Manufacturer: Expro3, LLC
Category: otc | Type: HUMAN OTC DRUG LABEL
Date: 20130307

ACTIVE INGREDIENTS: OATMEAL 1.25 g/125 g
INACTIVE INGREDIENTS: WATER; GLYCERIN; MEDIUM-CHAIN TRIGLYCERIDES; JOJOBA OIL; SHEA BUTTER; CETYL ALCOHOL; ALOE VERA LEAF; COMFREY LEAF; PHENOXYETHANOL; XANTHAN GUM; CAPRYLYL GLYCOL; CALENDULA OFFICINALIS FLOWER; LEVOMENOL; CHAMAEMELUM NOBILE FLOWER

Active Ingredient Purpose

Colloidal Oatmeal 0.1%............Skin Protectant

PURPOSE

Intensively Hydrates & Naturally Helps to Relieve Dry, Itchy, Irritated Skin due to Eczema & Rashes

Keep out of the reach of children

Uses:

Temporarily protects and helps relieve minor skin irritation and itching due to:

- eczema
- rashes

WARNINGS

For external use only

When using this product:

- do not get into eyes

Stop use and ask a doctor if:

- condition worsens
- symptoms last more than 7 days or clear up and occur again within a few days

If swallowed, get medical help or contact a Poison Control Center right away. (U.S. - 1-800-222-1222)

Directions:

- Apply liberally to dry, itchy patches and irritated skin, as often as necessary.
- Suitable for daily use.
- Delicate enough to use on newborn skin.

Other Information:

For use on mild to moderate excema or as directed by a physician. Store at room temperature.

Inactive Ingredients:

water (aqua), vegetable glycerin, caprylic/capric/triglyceride, simmondsia chinensis (jojoba) seed oil*, butyrospermum parkii (shea butter), cetyl alcohol, aloe vera barbadensis leaf juice*, symphytum officinale leaf extract, phenoxyethanol, xanthan gum, caprylyl glycol, calendula officinalis flower oil, avena sativa (oat) kernel extract, bisabolol, anthemis nobilis (chamomile) flower extract*.

*certified organic